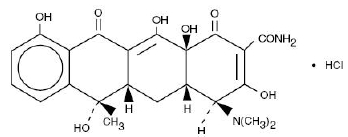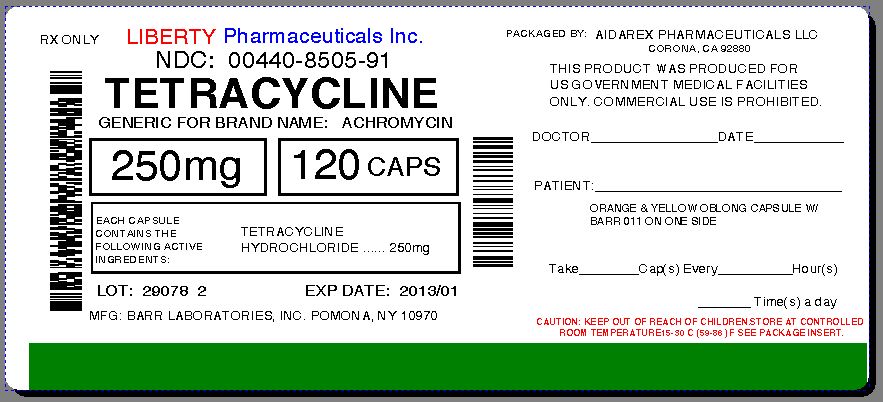 DRUG LABEL: Tetracycline Hydrochloride
NDC: 0440-8505 | Form: CAPSULE
Manufacturer: Liberty Pharmaceuticals, Inc.
Category: prescription | Type: HUMAN PRESCRIPTION DRUG LABEL
Date: 20130819

ACTIVE INGREDIENTS: TETRACYCLINE HYDROCHLORIDE 250 mg/1 1
INACTIVE INGREDIENTS: SILICON DIOXIDE; D&C YELLOW NO. 10; GELATIN; STARCH, CORN; PROPYLENE GLYCOL; SHELLAC; STEARIC ACID; TITANIUM DIOXIDE; FERROSOFERRIC OXIDE; FD&C BLUE NO. 1; ALUMINUM OXIDE; FD&C BLUE NO. 2; FD&C RED NO. 40; FD&C YELLOW NO. 6

TETRACYCLINE HYDROCHLORIDE CAPSULES USP

For Oral Use

Rx only

To reduce the development of drug-resistant bacteria and maintain the effectiveness of tetracycline hydrochloride and other antibacterial drugs, tetracycline hydrochloride should be used only to treat or prevent infections that are proven or strongly suspected to be caused by bacteria.

DESCRIPTION

Tetracycline is a yellow, odorless, crystalline powder. Tetracycline is stable in air but exposure to strong sunlight causes it to darken. Its potency is affected in solutions of pH below 2 and is rapidly destroyed by alkali hydroxide solutions. Tetracycline is very slightly soluble in water, freely soluble in dilute acid and in alkali hydroxide solutions, sparingly soluble in alcohol, and practically insoluble in chloroform and in ether. The chemical name for tetracycline hydrochloride is 4-(Dimethylamino)-1,4,4a,5,5a,6,11,12a-octahydro-3,6,10,12,-12a-pentahydroxy-6-methyl-1,11-dioxo-2-naphthacenecar-boxamide monohydrochloride. Its structural formula is as follows:

C22H24N208•HCI M.W. 480.90

Each capsule, for oral administration, contains 250 mg or 500 mg tetracycline hydrochloride, and has the following inactive ingredients: colloidal silicon dioxide, D&C Yellow #10, gelatin, pregelatinized starch, propylene glycol, shellac glaze (modified), stearic acid, and titanium dioxide. The 250 mg capsules also contain black iron oxide, FD&C Blue #1 Aluminum Lake, FD&C Blue #2 Aluminum Lake, FD&C Red #40 Aluminum Lake, and FD&C Yellow #6. The 500 mg capsules also contain ammonium hydroxide, FD&C Blue #1, FD&C Red #40, and simethicone.

CLINICAL PHARMACOLOGY

Tetracyclines are readily absorbed and are bound to plasma proteins in varying degrees. They are concentrated by the liver in the bile and excreted in the urine and feces at high concentrations in a biologically active form.

Microbiology

Tetracyclines are primarily bacteriostatic and exert their antimicrobial effect by the inhibition of protein synthesis. Tetracycline is active against a wide range of gram-negative and gram-positive organisms. The drugs in the tetracycline class have closely similar antimicrobial spectra, and cross-resistance among them is common. While in vitro studies have demonstrated the susceptibility of most strains of the following microorganisms, clinical efficacy for infections other than those included in the INDICATIONS AND USAGE section has not been documented.

Gram-negative Bacteria

Neisseria gonorrhea

Haemophilus ducreyi

Haemophilus influenzae

Yersinia pestis (formerly Pasteurella pestis)

Francisella tularensis (formerly Pasteurella tularensis)

Vibrio cholera (formerly Vibrio comma)

Bartonella bacilliformis

Brucella species

Because many strains of the following groups of gram-negative microorganisms have been shown to be resistant to tetracyclines, culture and susceptibility testing are recommended:

Escherichia coli

Klebsiella species

Enterobacter aerogenes

Shigella species

Acinetobacter species (formerly Mima species and Herellea species)

Bacteroides species

Gram-positive Bacteria

Because many strains of the following groups of gram-positive microorganisms have been shown to be resistant to tetracycline, culture and susceptibility testing are recommended. Up to 44 percent of strains of Streptococcus pyogenes and 74 percent of Streptococcus faecalis have been found to be resistant to tetracycline drugs. Therefore, tetracyclines should not be used for streptococcal disease unless the organisms have been demonstrated to be susceptible.

Streptococcus pyogenes

Streptococcus pneumoniae

Enterococcus group (Streptococcus faecalis and Streptococcus faecium)

Alpha-hemolytic Streptococci (viridans group)

Other microorganisms

Chlamydia psittaci

Chlamydia trachomatis

Ureaplasma urealyticum

Borrelia recurrentis

Treponema pallidum

Treponema pertenue

Clostridia species

Fusobacterium fusiforme

Actinomyces species

Bacillus anthraxis

Propionibacterium acnes

Entamoeba species

Balantidium coli

Susceptibility Testing

A tetracycline disk may be used to determine microbial susceptibility to drugs in the tetracycline class. If the Kirby-Bauer method of disk susceptibility testing is used, a 30 mcg tetracycline disk should give a zone of at least 19 mm when tested against a tetracycline susceptible bacterial strain. Microorganisms may be considered susceptible if the MIC (minimum inhibitory concentration) is not more than 4 mcg/mL and intermediate if the MIC is 4 to 12.5 mcg/mL.

INDICATIONS AND USAGE

To reduce the development of drug-resistant bacteria and maintain the effectiveness of tetracycline hydrochloride and other antibacterial drugs, tetracycline hydrochloride should be used only to treat or prevent infections that are proven or strongly suspected to be caused by susceptible bacteria. When culture and susceptibility information are available, they should be considered in selecting or modifying antibacterial therapy. In the absence of such data, local epidemiology and susceptibility patterns may contribute to the empiric selection of therapy.

Tetracycline is indicated in the treatment of infections caused by susceptible strains of the designated organisms in the conditions listed below:

- Upper respiratory tract infections caused by Streptococcus pyogenes, Streptococcus pneumoniae and Hemophilus influenzae. Note: Tetracycline should not be used for streptococcal disease unless the organism has been demonstrated to be susceptible.
- Lower respiratory tract infections caused by Streptococcus pyogenes, Streptococcus pneumoniae, Mycoplasma pneumoniae (Eaton agent, and Klebsiella sp.)
- Skin and soft tissue infections caused by Streptococcus pyogenes, Staphylococcus aureaus. (Tetracyclines are not the drugs of choice in the treatment of any type of staphylococcal infections.)
- Infections caused by rickettsia including Rocky Mountain spotted fever, typhus group infections, Q fever, rickettsialpox.
- Psittacosis or ornithosis caused by Chlamydia Psittaci.
- Infections caused by Chlamydia trachomatis such as uncomplicated urethral, endocervical or rectal infections, inclusion conjunctivitis, trachoma, and lymphogranuloma venereum.
- Granuloma inquinale caused by Calymmatobacterium granulomatis.
- Relapsing fever caused by Borrelia sp.
- Bartonellosis caused by Bartonella bacilliformis.
- Chancroid caused by Hemophilus ducreyi.
- Tularemia caused by Francisella tularensis.
- Plaque caused by Yersinia pestis.
- Cholera caused by Vibrio cholerae.
- Brucellosis caused by Brucella species (tetracycline may be used in conjunction with an aminoglycoside).
- Infections due to Campylobacter fetus.
- As adjunctive therapy in intestinal amebiasis caused by Entamoeba histolytica.
- Urinary tract infections caused by susceptible strains of Escherichia coli, Klebsiella, etc.
- Other infections caused by susceptible gram-negative organisms such as E. coli, Enterobacter aerogenes, Shigella sp., Acinetobacter sp., Klebsiella sp., and Bacteroides sp.
- In severe acne, adjunctive therapy with tetracycline may be useful.

When penicillin is contraindicated, tetracyclines are alternative drugs in the treatment of the following infections:

- Syphilis and yaws caused by Treponema pallidum and pertenue, respectively,
- Vincent’s infection caused by Fusobacterium fusiforme,
- Infections caused by Neisseria gonorrhoeae,
- Anthrax caused by Bacillus anthracis,
- Infections due to Listeria monocytogenes,
- Actinomycosis caused by Actinomyces species,
- Infections due to Clostridium species.

CONTRAINDICATIONS

This drug is contraindicated in persons who have shown hypersensitivity to any of the tetracyclines.

WARNINGS

THE USE OF DRUGS OF THE TETRACYCLINE CLASS DURING TOOTH DEVELOPMENT (LAST HALF OF PREGNANCY, INFANCY AND CHILDHOOD TO THE AGE OF 8 YEARS) MAY CAUSE PERMANENT DISCOLORATION OF THE TEETH (YELLOW - GRAY - BROWN). This adverse reaction is more common during long-term use of the drugs but has been observed following repeated short-term courses. Enamel hypoplasia has also been reported. TETRACYCLINE DRUGS, THEREFORE, SHOULD NOT BE USED IN THIS AGE GROUP UNLESS OTHER DRUGS ARE NOT LIKELY TO BE EFFECTIVE OR ARE CONTRAINDICATED.

All tetracyclines form a stable calcium complex in any bone forming tissue. A decrease in fibula growth rate has been observed in premature infants given oral tetracycline in doses of 25 mg/kg every six hours. This reaction was shown to be reversible when the drug was discontinued.

Results of animal studies indicate that tetracyclines cross the placenta, are found in fetal tissues and can have toxic effects on the developing fetus (often related to retardation of skeletal development). Evidence of embryotoxicity has also been noted in animals treated early in pregnancy. If this drug is used during pregnancy or if the patient becomes pregnant while taking this drug, the patient should be apprised of the potential hazard to the fetus. Tetracycline drugs should not be used during pregnancy unless absolutely necessary.

If renal impairment exists, even usual oral or parenteral doses may lead to excessive systemic accumulation of the drug and possible liver toxicity. Under such conditions, lower than usual total doses are indicated, and, if therapy is prolonged, serum level determinations of the drug may be advisable.

Photosensitivity manifested by an exaggerated sunburn reaction has been observed in some individuals taking tetracyclines. Patients apt to be exposed to direct sunlight or ultraviolet light should be advised that this reaction can occur with tetracycline drugs. Treatment should be discontinued at the first evidence of skin erythema.

The antianabolic action of the tetracyclines may cause an increase in BUN. While this is not a problem in those with normal renal function, in patients with significantly impaired renal function, higher serum levels of tetracycline may lead to azotemia, hyperphosphatemia and acidosis.

PRECAUTIONS

General

As with other antibiotics, use of this drug may result in overgrowth of nonsusceptible organisms, including fungi. If superinfection occurs, the antibiotic should be discontinued and appropriate therapy should be instituted.

All infections due to Group A beta-hemolytic streptococci should be treated for at least ten days.

Bulging fontanels in infants and benign intracranial hypertension in adults have been reported in individuals receiving tetracyclines. These conditions disappeared when the drug was discontinued.

Incision and drainage or other surgical procedures should be performed in conjunction with antibiotic therapy, when indicated.

Prescribing tetracycline in the absence of proven or strongly suspected bacterial infection or a prophylactic indication is unlikely to provide benefit to the patient and increases the risk of the development of drug-resistant bacteria.

Information for Patients

Patients should be counseled that antibacterial drugs including tetracycline should only be used to treat bacterial infections. They do not treat viral infections (e.g., the common cold). When tetracycline is prescribed to treat a bacterial infection, patients should be told that although it is common to feel better early in the course of therapy, the medication should be taken exactly as directed. Skipping doses or not completing the full course of therapy may (1) decrease the effectiveness of the immediate treatment and (2) increase the likelihood that bacteria will develop resistance and will not be treatable by tetracycline or other antibacterial drugs in the future.

Laboratory Tests

In venereal diseases, when coexistent syphilis is suspected, dark field examinations should be done before treatment is started and the blood serology repeated monthly for at least four months.

In long-term therapy, periodic laboratory evaluation of organ systems, including hematopoietic, renal and hepatic studies, should be performed.

Drug Interactions

Since bacteriostatic drugs may interfere with the bactericidal action of penicillin, it is advisable to avoid giving tetracycline in conjunction with penicillin or other bactericidal antibiotics.

Because the tetracyclines have been shown to depress plasma prothrombin activity, patients who are on anticoagulant therapy may require downward adjustment of their anticoagulant dosage.

The concurrent use of tetracycline and methoxyflurane has been reported to result in fatal renal toxicity.

Absorption of tetracyclines is impaired by antacids containing aluminum, calcium or magnesium and preparations containing iron, zinc, or sodium bicarbonate.

Concurrent use of tetracycline may render oral contraceptives less effective.

Carcinogenesis, Mutagenesis, Impairment of Fertility

Long-term animal studies are currently being conducted to determine whether tetracycline hydrochloride has carcinogenic potential. Some related antibiotics (oxytetracycline, minocycline) have shown evidence of oncogenic activity in rats.

In two in vitro mammalian cell assay systems (L 51784y mouse Iymphoma and Chinese hamster lung cells), there was evidence of mutagenicity at tetracycline hydrochloride concentrations of 60 and 10 mcg/mL, respectively.

Tetracycline hydrochloride had no effect on fertility when administered in the diet to male and female rats at a daily intake of 25 times the human dose.

Pregnancy

Teratogenic Effects:

Pregnancy Category D

(see WARNINGS)

Nonteratogenic Effects:

(see WARNINGS)

Pregnant women with renal disease may be more prone to develop tetracycline-associated liver failure.

Labor and Delivery

The effect of tetracyclines on labor and delivery is unknown.

Nursing Mothers

Because of the potential for serious adverse reaction in nursing infants from tetracyclines, a decision should be made whether to discontinue the drug, taking into account the importance of the drug to the mother (see WARNINGS).

Pediatric Use

See WARNINGS and DOSAGE AND ADMINISTRATION.

ADVERSE REACTIONS

Gastrointestinal: anorexia, nausea, epigastric distress, vomiting, diarrhea, glossitis, black hairy tongue, dysphagia, enterocolitis, and inflammatory lesions (with monilial overgrowth) in the anogenital region.

Rare instances of esophagitis and esophageal ulceration have been reported in patients receiving particularly the capsule and also the tablet forms of tetracyclines.

Most of the patients were reported to have taken medication immediately before going to bed (see DOSAGE AND ADMINISTRATION).

Teeth: permanent discoloration of teeth may be caused during tooth development. Enamel hypoplasia has also been reported (see WARNINGS).

Skin: maculopapular and erythematous rashes. Exfoliative dermatitis has been reported but is uncommon. Onycholysis and discoloration of the nails have been reported rarely. Photosensitivity is discussed in WARNINGS.

Renal toxicity: rise in BUN has been reported and is apparently dose related.

Liver: hepatotoxicity and liver failure have been observed in patients receiving large doses of tetracycline and in tetracycline-treated patients with renal impairment.

Hypersensitivity reactions: urticaria, angioneurotic edema, anaphylaxis, anaphylactoid purpura, pericarditis, exacerbation of systemic lupus erythematosus, and serum sickness-like reactions, as fever, rash, and arthralgia.

Blood: hemolytic anemia, thrombocytopenia, thrombocytopenic purpura, neutropenia and eosinophilia have been reported.

Other: bulging fontanels in infants and intracranial pressure in adults (see PRECAUTIONS, General).

When given over prolonged periods, tetracyclines have been reported to produce brown-black microscopic discoloration of thyroid glands. No abnormalities of thyroid function studies are known to occur.

OVERDOSAGE

In case of overdosage, discontinue medication, treat symptomatically and institute supportive measures. Tetracycline is not dialyzable.

DOSAGE AND ADMINISTRATION

Adults

Usual daily dose, 1 gram as 500 mg b.i.d. or 250 mg q.i.d. Higher doses such as 500 mg q.i.d. may be required for severe infections or for those infections which do not respond to the smaller doses.

Children above eight years of age

Usual daily dose, 10 to 20 mg/lb (25 to 50 mg/kg) body weight divided in four equal doses.

Therapy should be continued for at least 24 to 48 hours after symptoms and fever have subsided.

For treatment of brucellosis, 500 mg tetracycline q.i.d. for three weeks should be accompanied by streptomycin, 1 gram intramuscularly twice daily the first week and once daily the second week.

For the treatment of syphilis in patients allergic to penicillin, the following dosage of tetracycline is recommended: early syphilis (less than one year’s duration), 500 mg q.i.d. for 15 days. Syphilis of more than one year’s duration (except neurosyphilis), 500 mg q.i.d. for 30 days.

For treatment of gonorrhea, the recommended dose is 500 mg by mouth four times a day for seven days.

In cases of moderate to severe acne which, in the judgement of the clinician, require long-term treatment, the recommended initial dosage is 1 gram daily in divided doses. When improvement is noted, dosage should be gradually reduced to maintenance levels ranging from 125 mg to 500 mg daily. In some patients it may be possible to maintain adequate remission of lesions with alternate-day or intermittent therapy. Tetracycline therapy of acne should augment the other standard measures known to be of value. Duration of long-term treatment which can safely be recommended has not been established (see WARNINGS and Carcinogenesis, Mutagenesis, Impairment of Fertility).

Concomitant therapy

Absorption of tetracycline is impaired by antacids containing aluminum, calcium or magnesium and preparations containing iron, zinc, or sodium bicarbonate.

Food and some dairy products also interfere with absorption.

In the treatment of streptococcal infections, a therapeutic dose of tetracycline should be administered for at least ten days.

In patients with renal impairment (see WARNINGS): total dosage should be decreased by reduction of recommended individual doses and/or by extending time intervals between doses.

Uncomplicated urethral, endocervical or rectal infections in adults caused by Chlamydiatrachomatis: 500 mg, by mouth, four times a day for at least seven days.

Administration of adequate amounts of fluid with the capsule formulation of tetracycline is recommended to wash down the drug and reduce the risk of esophageal irritation and ulceration (see ADVERSE REACTIONS).

HOW SUPPLIED

Tetracycline Hydrochloride Capsules USP, 250 mg are available as orange opaque and yellow opaque capsules, imprinted with “Z” and “2416” in black ink, containing 250 mg of tetracycline hydrochloride, packaged in bottles of 100 and 1000 capsules, and unit-dose boxes of 100 capsules.

Tetracycline Hydrochloride Capsules USP, 500 mg are available as black and yellow capsules, imprinted with “Z” and “2407” in white ink, containing 500 mg of tetracycline hydrochloride, packaged in bottles of 100 and 1000 capsules, and unit-dose boxes of 100 capsules.

Dispense in a tight, light resistant container as defined in the USP, with a child-resistant closure (as required).

Store at 20° to 25°C (68° to 77°F) [See USP Controlled Room Temperature].

ANIMAL PHARMACOLOGY AND ANIMAL TOXICOLOGY

Hyperpigmentation of the thyroid has been produced by members of the tetracycline class in the following species: in rats by oxytetracycline, doxycycline, minocycline, tetracycline PO4 and methacycline; in minipigs by doxycycline, minocycline, tetracycline PO4 and methacycline; in dogs by doxycycline and minocycline; in monkeys by minocycline.

Minocycline, tetracycline PO4, methacycline, doxycycline, tetracycline base, oxytetracycline HCI and tetracycline HCI were goitrogenic in rats fed a low iodine diet. This goitrogenic effect was accomplished by high radioactive iodine uptake. Administration of minocycline also produced a large goiter with high radioiodine uptake in rats fed a relatively high iodine diet.

Treatment of various animal species with this class of drugs has also resulted in the induction of thyroid hyperplasia in the following: in rats and dogs (minocycline), in chickens (chlortetracycline) and in rats and mice (oxytetracycline). Adrenal gland hyperplasia has been observed in goats and rats treated with oxytetracycline.

TEVA PHARMACEUTICALS USA

Sellersville, PA 18960

Rev. B 3/2011

Repackaged By:
Aidarex Pharmaceuticals, LLC
Corona, CA 92880

PRINCIPAL DISPLAY PANEL

Tetracycline Hydrochloride Capsules USP 250 mg 100s Label Text

NDC 0440-8505-91

TETRACYCLINE

HYDROCHLORIDE

Capsules USP

250 mg

Rx only

100 CAPSULES